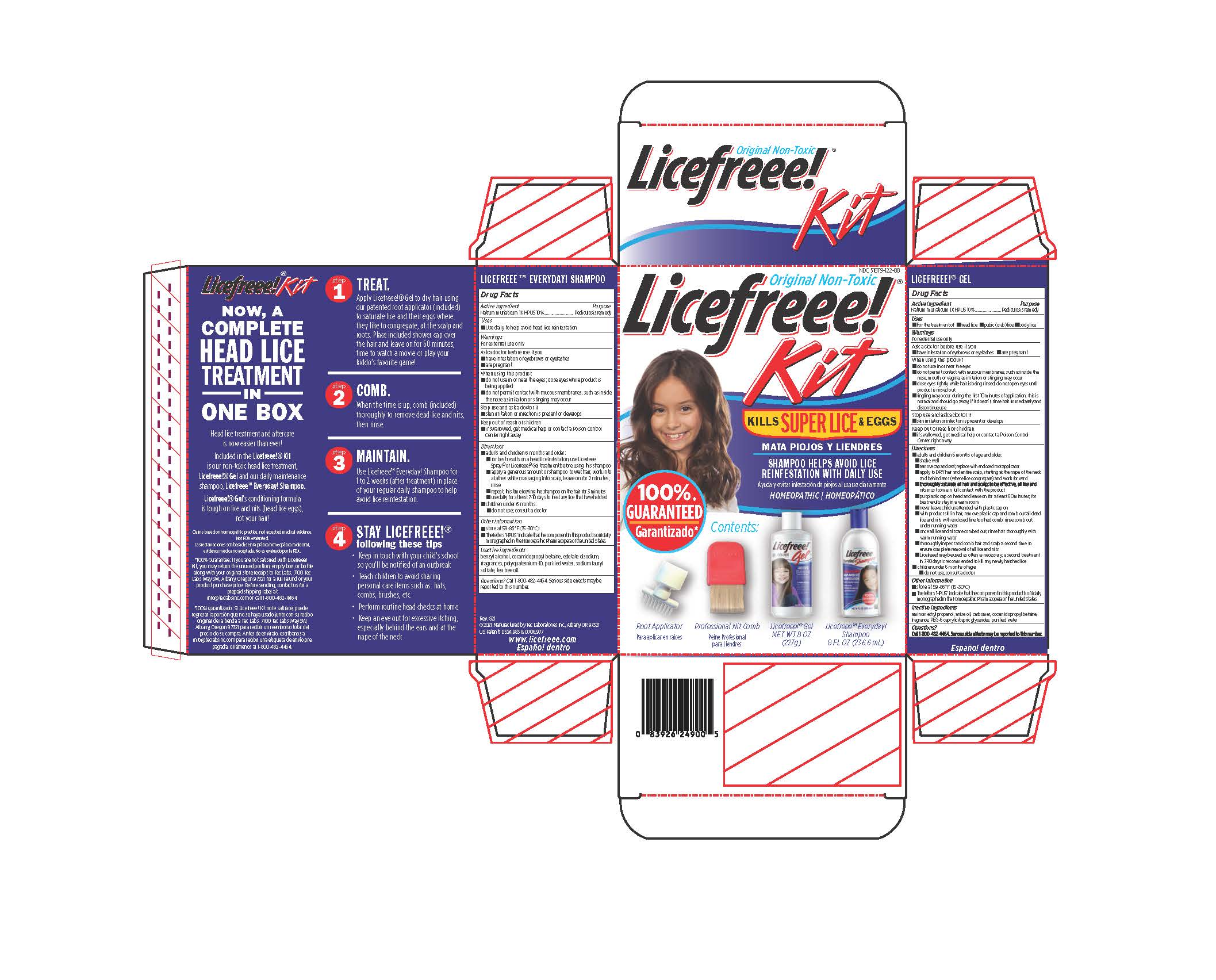 DRUG LABEL: Licefreee
NDC: 51879-122 | Form: KIT | Route: TOPICAL
Manufacturer: Tec Laboratories, Inc.
Category: homeopathic | Type: HUMAN OTC DRUG LABEL
Date: 20241105

ACTIVE INGREDIENTS: SODIUM CHLORIDE 1 [hp_X]/1 g; SODIUM CHLORIDE 1 [hp_X]/1 mL
INACTIVE INGREDIENTS: WATER; COCAMIDOPROPYL BETAINE; AMINOMETHYL PROPANEDIOL; PEG-6 CAPRYLIC/CAPRIC GLYCERIDES; CARBOMER HOMOPOLYMER TYPE C (ALLYL PENTAERYTHRITOL CROSSLINKED); ANISE OIL; BENZYL ALCOHOL; WATER; COCAMIDOPROPYL BETAINE; TEA TREE OIL; POLYQUATERNIUM-10 (125 MPA.S AT 2%); EDETATE DISODIUM; SODIUM LAURYL SULFATE

LiceFreee Kit

Licefreee Shampoo Everyday!

Active Ingredient

Natrum muriaticum 1X 10% HPUS (Sodium chloride)

Purpose

Pediculosis remedy

Uses

- Use daily to help avoid head lice reinfestation.

Warnings

For external use only.

Ask a doctor before use if you

- have infestation of eyebrows or eyelashes
- are pregnant

When using this product

- do not use in or near the eyes; close eyes while product is being applied
- do not permit contact with mucous membranes, such as inside the nose as irritation or stinging may occur

Stop use and ask a doctor if

- skin irritation or infection is present or develops

Keep out of reach of children

- if swallowed, get medical help or contact a Poison Control Center right away

Directions

- Adults and children 6 months and older:
- for best results on a head lice infestation, use Licefreee Spray!® or Licefreee!® Gel treatment before using this shampoo.
- apply a generous amount of shampoo to wet hair, work into a lather while massaging into scalp; rinse
- repeat, this time leaving the shampoo on the hair for 3 minutes; rinse
- use daily for at least 7-10 days to treat any lice that have hatched.
- Children under 6 months:
- do not use; consult a doctor

Other information

store at 59-86°F (15-30°C)

Inactive ingredients

benzyl alcohol, cocamidopropyl betaine, disodium EDTA, fragrances, polyquaternium 10, purified water, sodium lauryl sulfate, tea tree oil

Questions?

Call 1-800-482-4464. Serious side effects may be reported to this number.

Licefreee! Gel Lice Treatment

Active Ingredient

Natrum muriaticum 1X 10% HPUS (Sodium chloride)

Purpose

Pediculosis remedy

Uses

■For the treatment of ■ head lice ■ pubic (crab) lice ■ body lice

Warnings

For external use only

Ask a doctor before use if you have

- infestation of eyebrows or eyelashes

When using this product

- do not use in or near the eyes
- do not permit contact with mucous membranes, such as inside the nose, mouth, or vagina, as irritation or stinging may occur
- close eyes tightly while hair is being rinsed; do not open eyes until product is rinsed out
- tingling may occur during the first 10 minutes of application; this is normal and should go away; if it doesn’t, rinse hair immediately and discontinue use

Stop use and ask a doctor if

- skin irritation or infection is present or develops

Keep out of reach of children

- if swallowed, get medical help or contact a Poison Control Center right away.

Directions

- adults and children 6 months of age and older:
- shake well
- remove cap and tamper evident seal; replace with enclosed root applicator
- apply to DRY hair and entire scalp, starting at the nape of the neck and behind ears (where lice congregate) and work forward
- thoroughly saturate all hair and scalp; to be effective, all lice and nits must come in full contact with the product
- put plastic cap on head and leave on for at least 60 minutes; for best results stay in a warm room
- never leave child unattended with plastic cap on
- with product still in hair, remove plastic cap and comb out all dead lice and nits with enclosed fine toothed comb; rinse comb out under running water
- once all lice and nits are combed out, rinse hair thoroughly with warm running water
- thoroughly inspect and comb hair and scalp a second time to ensure complete removal of all lice and nits
- Licefreee! may be used as often as necessary; a second treatment in 7-10 days is recommended to kill any newly hatched lice
- children under 6 months of age:
- do not use, consult a doctor

Other Information

Store at 59 - 86°F (15 - 30°C)

Inactive Ingredients

aminomethyl propanol, anise oil, carbomer, cocamidopropyl betaine, fragrance, PEG-6 caprylic/capric glycerides, purified water

Questions?

Call 1-800-482-4464. Serious side effects can be reported to this number.

RECENT MAJOR CHANGES

- repeat this time leaving the shampoo on the hair 3 minutes

PACKAGE LABEL

NDC 51879-122-88

Original Non-Toxic

Licefreee! Kit

Includes:

Licefreee!® Gel Head Lice Treatment

Licefreee® Everyday! Shampoo

KILLS SUPER LICE and EGGS

MATA PIOJOS Y LIENDRES

Shampoo helps Avoid Lice Reinfestation with daily use

Ayuda y evitar infestación de

piojos al usarse diariamente

Homeopathic

Homeopática

CONTENTS:

Homeopathic

Homeopática

CONTENTS:

Licefreee Gel NET WT 8 OZ (227g)

Licefreee Shampoo NET 8 FL OZ (236.6 mL)

Professional Nit Comb

Piene Profesional para Liendres